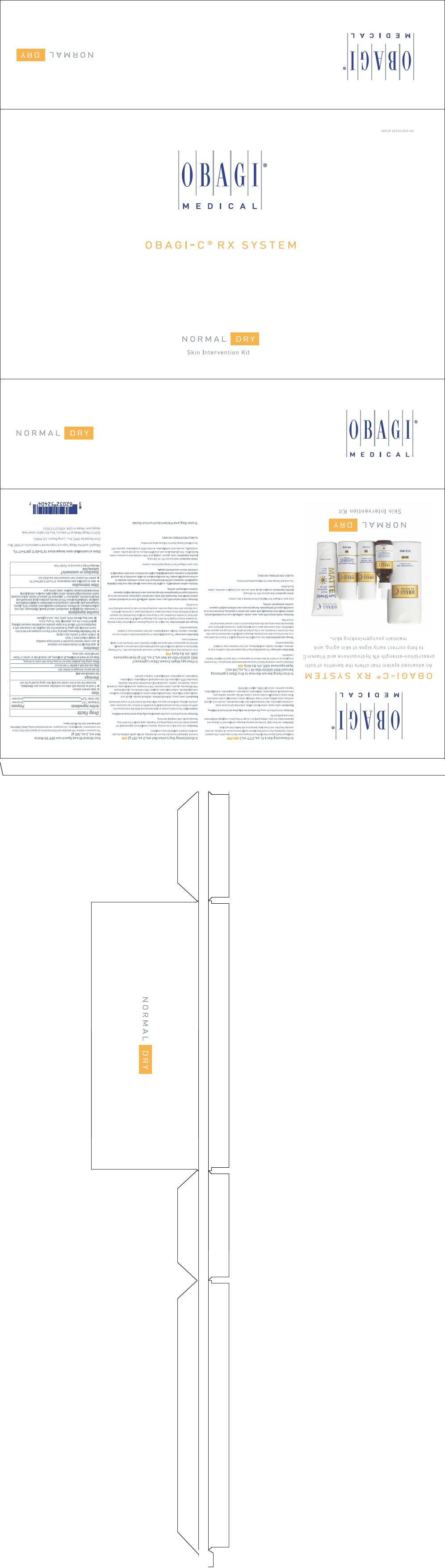 DRUG LABEL: OBAGI-C RX SYSTEM NORMAL-DRY
NDC: 62032-524 | Form: KIT | Route: TOPICAL
Manufacturer: OMP, INC.
Category: prescription | Type: HUMAN PRESCRIPTION DRUG LABEL
Date: 20130812

ACTIVE INGREDIENTS: HYDROQUINONE 40 mg/1 mL; HYDROQUINONE 40 mg/1 g; OCTINOXATE 75 mg/1 g; ZINC OXIDE 105 mg/1 g
INACTIVE INGREDIENTS: PROPYLENE GLYCOL; WATER; ASCORBIC ACID; SODIUM LAURYL SULFATE; PROPYLENE CARBONATE; EDETATE DISODIUM; PPG-2 MYRISTYL ETHER PROPIONATE; TROLAMINE SALICYLATE; SODIUM LAURYL SULFATE; CETYL ALCOHOL; GLYCERIN; LACTIC ACID; .ALPHA.-TOCOPHEROL ACETATE; ASCORBIC ACID; SODIUM METABISULFITE; WATER; METHYLPARABEN; PROPYLPARABEN; BUTYLATED HYDROXYTOLUENE; PHENYL TRIMETHICONE; GLYCERIN; PHENOXYETHANOL; CYCLOMETHICONE 5; WATER; PEG-10 DIMETHICONE (600 CST); PENTYLENE GLYCOL; STEARYL ALCOHOL; POLYOXYL 20 CETOSTEARYL ETHER; PHENYL TRIMETHICONE; PEG-40 STEARATE; DIMETHICONE; SODIUM DIHYDROXYCETYL PHOSPHATE; HYDROGENATED PALM GLYCERIDES; CITRIC ACID MONOHYDRATE; CETOSTEARYL ALCOHOL; .ALPHA.-TOCOPHEROL ACETATE; 1,2-HEXANEDIOL; CAPRYLYL GLYCOL; TROPOLONE; CHLORPHENESIN; XANTHAN GUM; POTASSIUM SORBATE; SODIUM BENZOATE; TETRAHEXYLDECYL ASCORBATE; UBIDECARENONE; EDETATE DISODIUM; METHYLISOTHIAZOLINONE; HYDROXYETHYL ACRYLATE/SODIUM ACRYLOYLDIMETHYL TAURATE COPOLYMER (45000 MPA.S AT 1%); SQUALANE; POLYSORBATE 60; SODIUM POLYACRYLATE (2500000 MW)

OBAGI-C® RX SYSTEM NORMAL-DRY
SKIN INTERVENTION KIT

C-Cleansing Gel 6 fl. oz. (177 mL.) AM+PM

A gel-based facial cleanser that clarifies and prepares your skin for absorption of the system's product ingredients. This concentrated cleanser gently removes excess oil, makeup, and other everyday impurities, and rinses clean, leaving your skin feeling fresh and clear.

Directions

Use twice daily, morning and evening. Massage a small amount of cleanser and lukewarm water onto skin, rubbing gently in a circular motion. Rinse completely with lukewarm water and gently pat dry.

Warnings

Avoid getting into eyes. For external use only.

Keep out of reach of children.

Ingredients

water (aqua), sodium laureth sulfate, sodium lauroyl oat amino acids, cocamidopropyl betaine, aloe barbadensis leaf juice (aloe barbadensis), ascorbic acid, glycerin, medicago sativa (alfalfa) extract, borago officinalis extract, chamomilla recutita (matricaria) flower extract (chamomilla recutita extract), sodium chloride, saponins, xanthan gum, phenoxyethanol, methylparaben, ethylparaben, butylparaben, propylparaben, isobutylparaben, fragrance (parfum), red 33 (CI 17200), yellow 5 (CI 19140)

C-Clarifying Serum Normal to Dry (Skin Lightening Serum) NDC 62032-106-10 1 fl. oz. (30 mL.) Hydroquinone USP, 4% Rx Only AM

Antioxidant serum containing Vitamin C and prescription-strength hydroquinone. This patented formulation for normal to dry skin reduces the appearance of dark spots for a lighter, brighter complexion.

Indications and usage

The gradual bleaching of hyperpigmented skin conditions such as chloasma, melasma, freckles, senile lentigines, and other unwanted areas of melanin hyperpigmentation.

Dosage and administration

Use once daily in the morning. Apply 5-7 drops to the entire face, or as directed by your skin care physician. Massage in gently. If no improvement is seen after three (3) months of treatment, use of this product should be discontinued. Sun exposure should be limited by using a sunscreen agent, a sun blocking agent, or protective clothing to cover bleached skin when using and after using this product in order to prevent darkening from reoccurring.

Warnings

DO NOT USE

Avoid contact with eyes, nose, mouth, or lips. In case of accidental contact, patient should rinse eyes thoroughly with water and contact physician. Sunscreen use is an essential aspect of hydroquinone therapy because even minimal sunlight exposure sustains melanocytic activity.

Each gram of Obagi-C Rx C-Clarifying Serum Normal to Dry contains:

Active Ingredient

Hydroquinone USP, 4% (40 mg/g)

Inactive Ingredients

propylene glycol, water, ascorbic acid, propylene carbonate, sodium lauryl sulfate.

See enclosed Package Insert for full prescribing information.

Rx ONLY. FOR EXTERNAL USE ONLY.

C-Exfoliating Day Lotion Net wt. 2 oz. (57 g.) AM

A smooth, lightweight moisturizer that not only hydrates, but also gently exfoliates the skin, revealing a brighter, healthier-looking complexion.

Directions

Use once daily in the morning. Squeeze a small amount (approximately 1-2 pea-sized drops) onto your hands. Using your fingertips, apply evenly to the entire face. Massage gently until completely absorbed.

Warnings

Avoid getting into eyes. For external use only.

Keep out of reach of children.

Sunburn Alert

This product contains an alpha hydroxy acid (AHA) that may increase your skin's sensitivity to the sun and particularly the possibility of sunburn. Use a sunscreen, wear protective clothing, and limit sun exposure while using this product and for a week afterwards.

Ingredients

water (aqua), ethylhexyl palmitate, ethylhexyl stearate, glycolic acid, caprylic/capric triglyceride, hydroxyethyl acrylate/sodium acryloyldimethyl taurate copolymer, isopropyl palmitate, sodium hyaluronate, squalane, PEG-8 dimethicone, glyceryl stearate, PEG-100 stearate, glycerin, sodium hydroxide, PEG-8 ricinoleate, ascorbyl glucoside, tocopheryl acetate, dimethicone, arginine, cetearyl alcohol, ceteareth-20, steareth-2, bisabolol, tetrasodium EDTA, polysorbate 60, phenoxyethanol, methylparaben, ethylparaben, butylparaben, propylparaben, isobutylparaben, fragrance (parfum)

C-Therapy Night Cream (Skin Lightener) NDC 62032-105-36 Net wt. 2 oz. (57 g.) Hydroquinone USP, 4% Rx Only PM

A rich moisturizer that works while you sleep to renew and rejuvenate your skin. The C-Therapy Night Cream is uniquely formulated with prescription-strength hydroquinone to gradually diminish the appearance of dark spots and delivers Vitamins C and E during the skin's nightly renewal process.

Indications and usage

The gradual bleaching of hyperpigmented skin conditions such as chloasma, melasma, freckles, senile lentigines, and other unwanted areas of melanin hyperpigmentation.

Dosage and administration

Use daily in the evening. Dispense a small amount (approximately 1-2 pea-sized drops) and apply to the entire face. Massage in gently. If no improvement is seen after three (3) months of treatment, use of this product should be discontinued. Sun exposure should be limited by using a sunscreen agent, a sun blocking agent, or protective clothing to cover bleached skin when using and after using this product in order to prevent darkening from reoccurring.

Warnings

DO NOT USE

Avoid contact with eyes, nose, mouth, or lips. In case of accidental contact, patient should rinse eyes thoroughly with water and contact physician. Sunscreen use is an essential aspect of hydroquinone therapy because even minimal sunlight exposure sustains melanocytic activity.

Contains sodium metabisulfite, a sulfite that may cause allergic-type reactions including anaphylactic symptoms and life-threatening or less severe asthmatic episodes in certain susceptible people. The overall prevalence of sulfite sensitivity in the general population is unknown and probably low. Sulfite sensitivity is seen more frequently in asthmatic than in nonasthmatic people.

Each gram of Obagi-C Rx C-Therapy Night Cream contains:

Active Ingredient

Hydroquinone USP, 4% (40 mg/g)

Inactive Ingredients

water, glycerin, cetyl alcohol, PPG-2 myristyl ether propionate, sodium lauryl sulfate, TEA-salicylate, lactic acid, phenyl trimethicone, tocopheryl acetate, sodium metabisulfite, ascorbic acid, methylparaben, disodium EDTA, propylparaben, saponins, BHT

See enclosed Package Insert for full prescribing information.

Rx ONLY. FOR EXTERNAL USE ONLY.

Travel Bag and Patient Instruction Guide

Sun Shield Broad Spectrum SPF 50 Matte Net wt. 3 oz. (85 g)

This sunscreen combines UVB absorption and UVA protection in an elegant matte finish that is non-comedogenic, hypoallergenic, non-acnegenic, and dermatologist tested. Sheer, PABA free, and fragrance free for all skin types.

Drug Facts

ACTIVE INGREDIENT

Active ingredients | Purpose
Octinoxate 7.5% | Sunscreen
Zinc Oxide 10.5% | Sunscreen

Uses

- helps prevent sunburn
- if used as directed with other sun protection measures (see Directions), decreases the risk of skin cancer and early skin aging caused by the sun

Warnings

For external use only

Do not use on damaged or broken skin

Stop use and ask a doctor if rash occurs

When using this product keep out of eyes. Rinse with water to remove.

Keep out of reach of children. If swallowed, get medical help or contact a Poison Control Center right away.

Directions

- apply liberally 15 minutes before sun exposure
- use a water resistant sunscreen if swimming or sweating
- reapply at least every 2 hours
- children under 6 months: Ask a doctor
- Sun Protection Measures. Spending time in the sun increases your risk of skin cancer and early skin aging. To decrease this risk, regularly use a sunscreen with a Broad Spectrum SPF value of 15 or higher and other sun protection measures including:
  - limit time in the sun, especially from 10 a.m.–2 p.m.
  - wear long-sleeved shirts, pants, hats, and sunglasses

Inactive ingredients

1,2-hexanediol, caprylyl glycol, ceteareth-20, cetearyl alcohol, chlorphenesin, citric acid, cyclopentasiloxane, dimethicone, dimethicone crosspolymer-3, disodium EDTA, glycerin, hydrogenated palm glycerides, hydroxyethyl acrylate/sodium acryloyldimethyl taurate copolymer, methylisothiazolinone, PEG-40 stearate, pentylene glycol, phenoxyethanol, phenyl trimethicone, polysilicone-11, polysorbate 60, potassium sorbate, sodium benzoate, sodium dihydroxycetyl phosphate, sodium polyacrylate, squalane, stearyl alcohol, tetrahexyldecyl ascorbate, tropolone, water, xanthan gum

Other information

- store at controlled room temperature: 15°C–25°C (59°F–77°F)
- protect this product from excessive heat and direct sun

Questions or comments?

1.800.636.7546
Monday–Friday 9 a.m.–4 p.m. Pacific Time

STORAGE AND HANDLING

Store at controlled room temperature 15°C–25°C (59°F–77°F).

Obagi-C and the Obagi logo are registered trademarks of OMP, Inc.

Distributed by OMP, Inc., Long Beach, CA 90806

©2012 Obagi Medical Products, Inc. All rights reserved.
obagi.com Made in USA 41502211Z 5022

PRINCIPAL DISPLAY PANEL - Kit Carton

NDC# 62032-524-04

OBAGI®
MEDICAL

OBAGI-C® RX SYSTEM

NORMAL DRY
Skin Intervention Kit